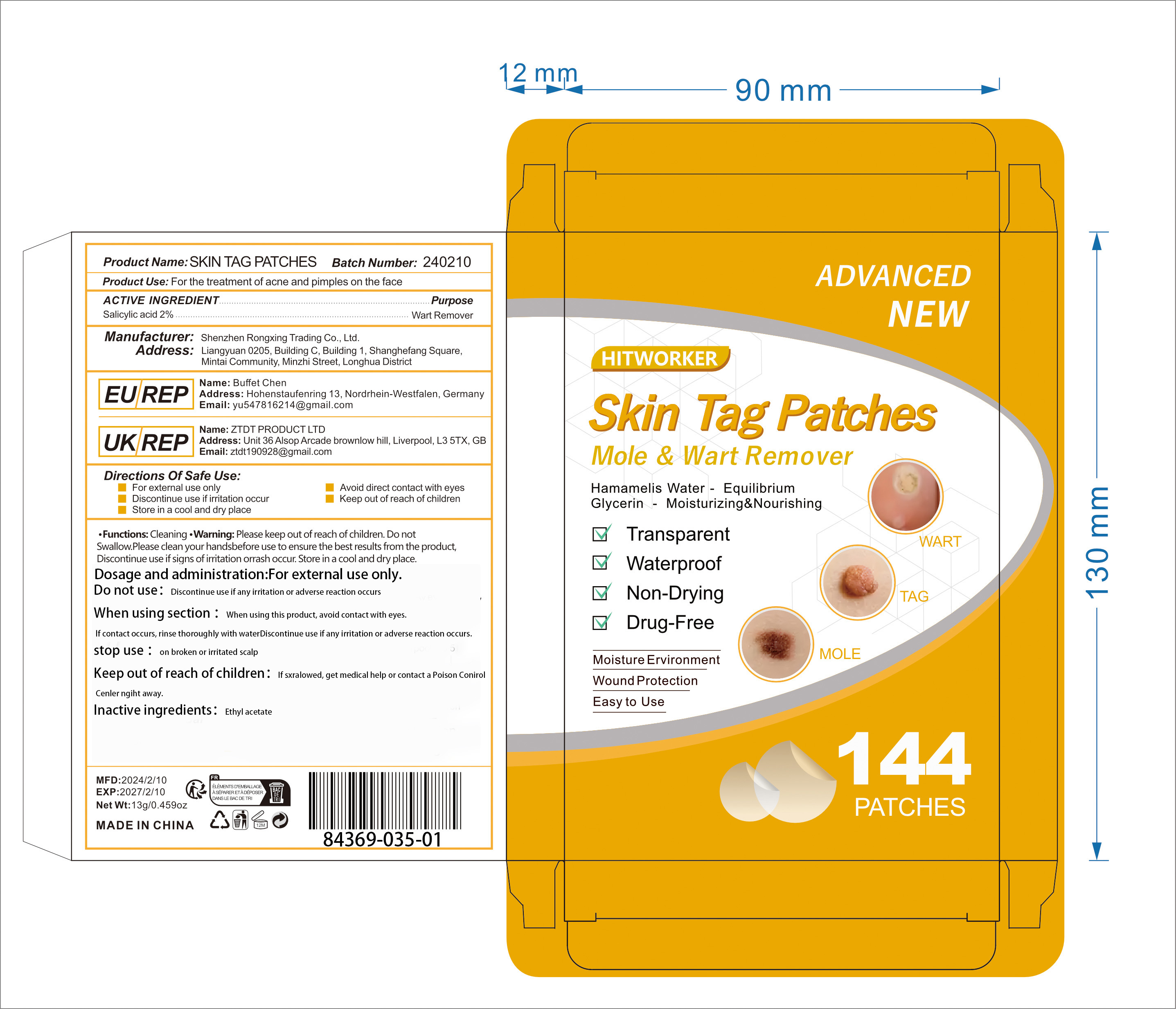 DRUG LABEL: Skin tag patches
NDC: 84369-035 | Form: PATCH
Manufacturer: Shenzhen Rongxing Trading Co., Ltd.
Category: otc | Type: HUMAN OTC DRUG LABEL
Date: 20240715

ACTIVE INGREDIENTS: SALICYLIC ACID 2 g/100 g
INACTIVE INGREDIENTS: ETHYL ACETATE

ACTIVE INGREDIENT

Salicylic acid 2%

Directions ofsafe Use

For external use only
Avoid direct contact with eyes
Discontinue use if irritation occur
Keep out ofreach of children
Store in a cool and dry place

Product Use

For the treatment of acne and pimples on the face

Warning

Please keep out of reach of children.Do not
Swallow.Please clean yourhandsbefore use to ensure the best results from the product
Discontinue useif signs ofirritationorrashoccur Store in a cooland dry place.

Dosage and administration

For external use only.

Do not use

Discontinue use if any irritation or adverse reaction occurs

Dosage and administration

For external use only.

Do not use

Discontinue use if any irritation or adverse reaction occurs

When using section

When using this product, avoid contact with eyes. lf contact occurs, rinse thoroughly with waterDiscontinue use if any irritation or adverse reaction occurs.

stop use

on broken or irritated scalp

Keep out of reach of children.

If sxralowed, get medical help or contact a Poison Conirol Cenler ngiht away.

Inactive ingredients

Ethyl acetate